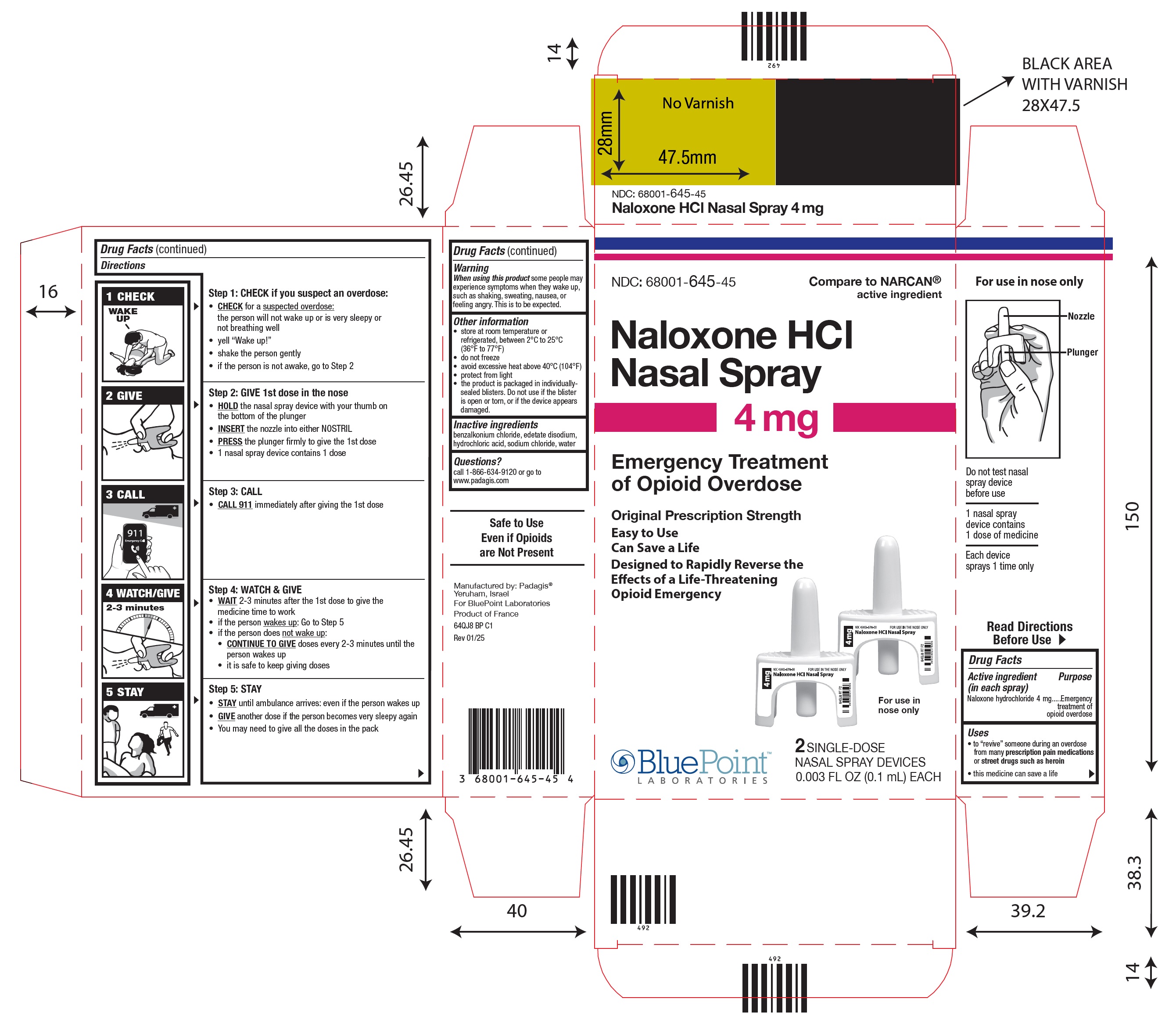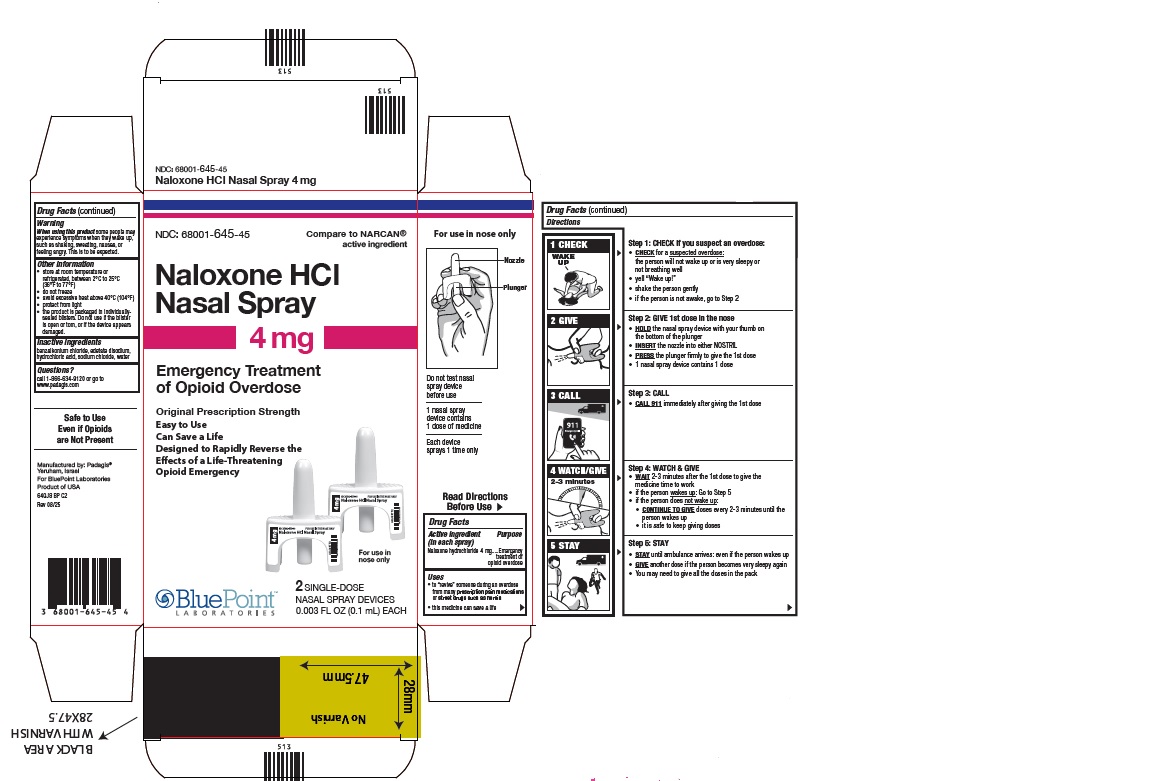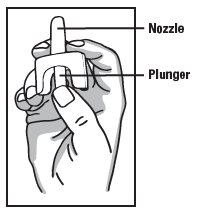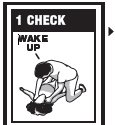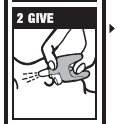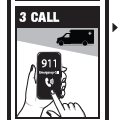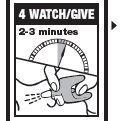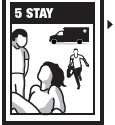 DRUG LABEL: NALOXONE HYDROCHLORIDE
NDC: 68001-645 | Form: SPRAY
Manufacturer: BluePoint Laboratories
Category: otc | Type: HUMAN OTC DRUG LABEL
Date: 20251008

ACTIVE INGREDIENTS: NALOXONE HYDROCHLORIDE 4 mg/0.1 mL
INACTIVE INGREDIENTS: BENZALKONIUM CHLORIDE; EDETATE DISODIUM; SODIUM CHLORIDE; HYDROCHLORIC ACID; WATER

Naloxone HCl Nasal Spray Drug Facts

Active Ingredient (in each spray)

Naloxone hydrochloride 4 mg

Purpose

Emergency treatment of opioid overdose

Uses

• to “revive” someone during an overdose from many prescription pain medicationsor street drugs such as heroin

• this medicine can save a life

Directions

Emergency Treatment of Opioid Overdose

Important:

- For use in the nose only
- Do not test nasal spray device before use
- 1 nasal spray device contains 1 dose of medicine
- Each device sprays 1 time only

Do not test nasal spray device before use

1 nasal spray device contains 1 dose of medicine

Each device sprays 1 time only

Step 1: CHECK if you suspect an overdose:

• CHECKfor a suspected overdose: the person will not wake up or is very sleepy or not breathing well

•yell “Wake up!”

•shake the person gently

•if the person is not awake, go to Step 2

Step 2: GIVE 1st dose in the nose

• HOLDthe nasal spray device with your thumb on the bottom of the plunger

• INSERTthe nozzle into either NOSTRIL

• PRESSthe plunger firmly to give the 1st dose

•1 nasal spray device contains 1 dose

Step 3: CALL

• CALL 911immediately after giving the 1st dose

Step 4: WATCH & GIVE

• WAIT2-3 minutes after the 1st dose to give the medicine time to work

•if the person wakes up: Go to Step 5

•if the person does not wake up:

• CONTINUE TO GIVEdoses every 2-3 minutes until the person wakes up

•it is safe to keep giving doses

Step 5: STAY

• STAYuntil ambulance arrives: even if the person wakes up

• GIVEanother dose if the person becomes very sleepy again

•You may need to give all the doses in the pack

For opioid emergencies, call 911. For questions on Naloxone HCl Nasal Spray 4 mg, call Padagis® at 1-866-634-9120 or go to www.padagis.com.

64Q00 RT QS2

Warning

When using this productsome people may experience symptoms when they wake up, such as shaking, sweating, nausea, or feeling angry. This is to be expected

Other information

•store at room temperature or refrigerated, between 2°C to 25°C (36°F to 77°F)

•do not freeze

•avoid excessive heat above 40°C (104°F)

•protect from light

•the product is packaged in individually-sealed blisters.

Do not use if the blister is open or torn, or if the device appears damaged

Inactive Ingredients

benzalkonium chloride, edetate disodium, hydrochloric acid, sodium chloride, water

Questions?

- call 1-866-634-9120 or go to www.padagis.com

Package/Label Principal Display Panel

NDC 68001-645-45

Naloxone HCl Nasal Spray 4 mg

Emergency Treatment of Opioid Overdose

Original Prescription Strength

Easy to Use

Can Save a Life

Designed to Rapidly Reverse the Effects of a Life-Threatening Opioid Emergency

For use in nose only

2 SINGLE-DOSE NASAL SPRAY DEVICES

0.003 FL OZ (0.1mL) EACH

Rev 01/2025

NDC 68001-645-45

Naloxone HCl Nasal Spray 4 mg

Emergency Treatment of Opioid Overdose

Original Prescription Strength

Easy to Use

Can Save a Life

Designed to Rapidly Reverse the Effects of a Life-Threatening Opioid Emergency

For use in nose only

2 SINGLE-DOSE NASAL SPRAY DEVICES

0.003 FL OZ (0.1mL) EACH

Rev 08/2025